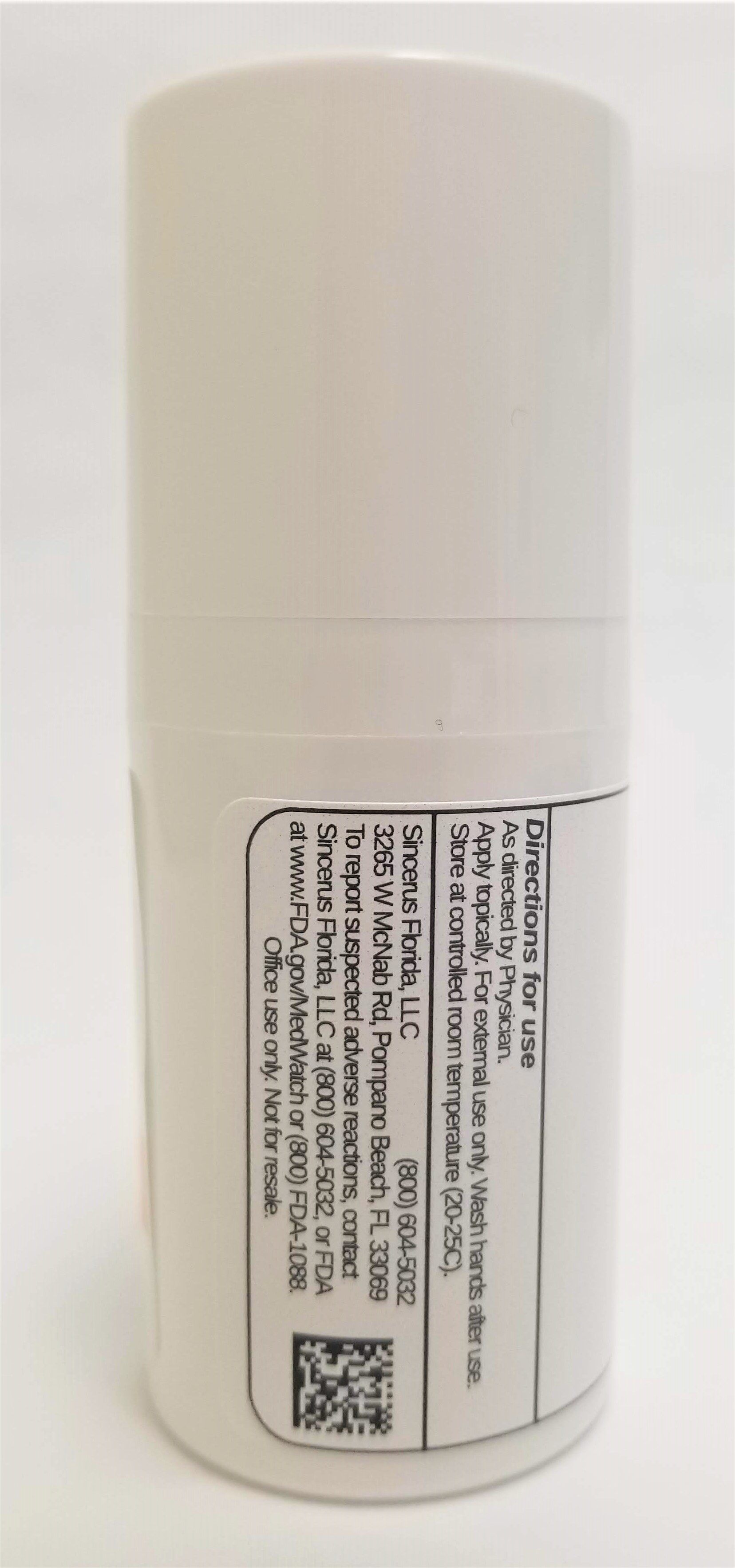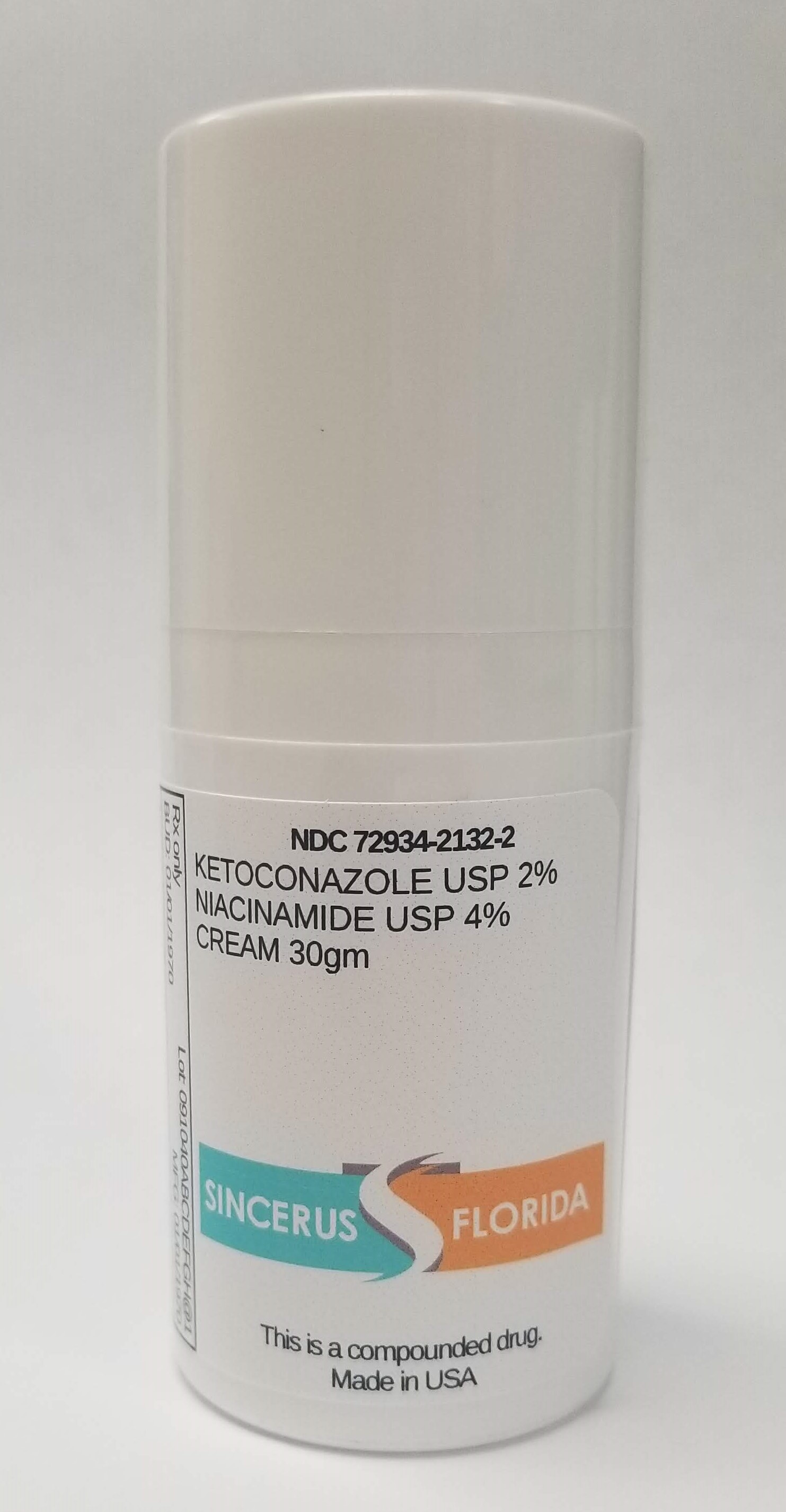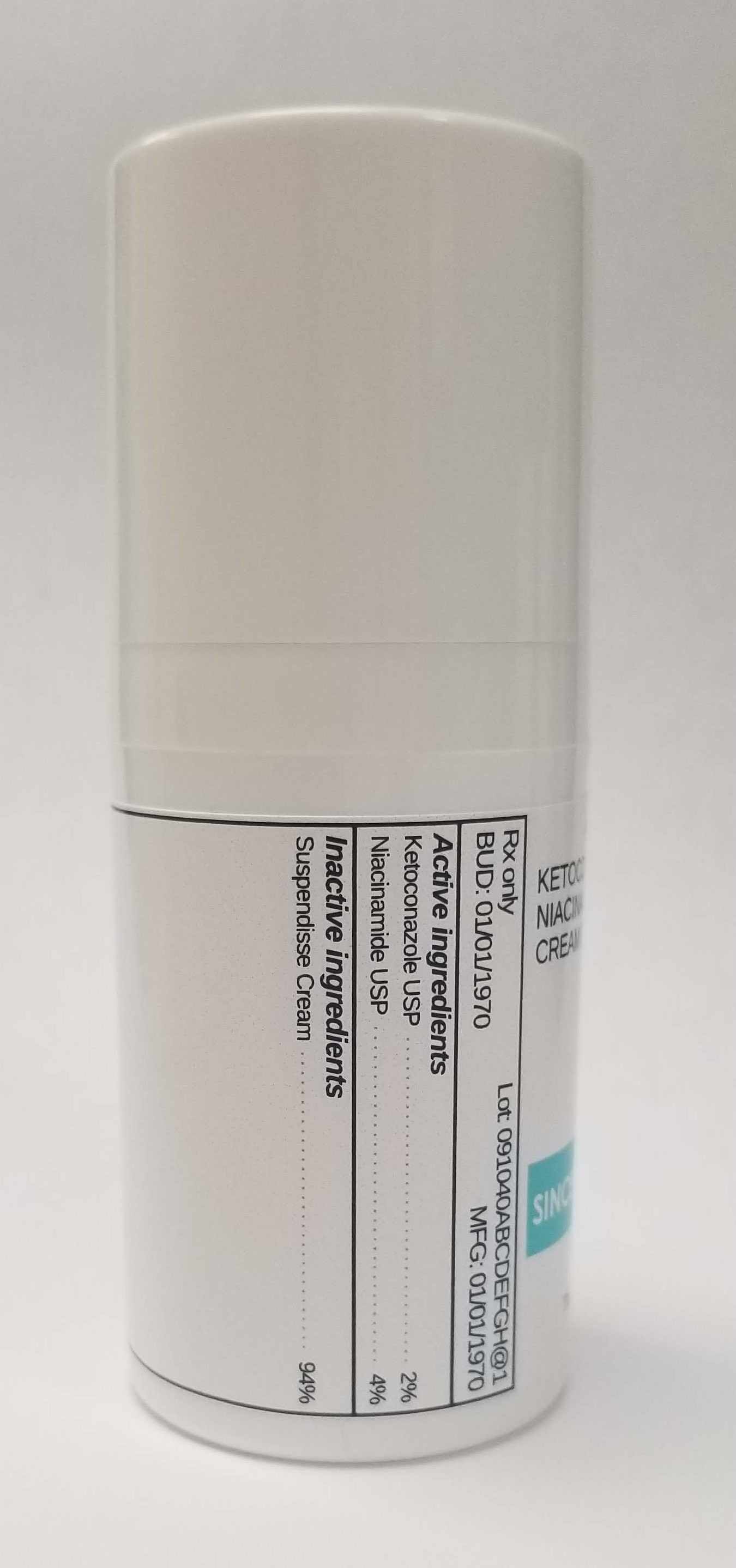 DRUG LABEL: KETOCONAZOLE 2% / NIACINAMIDE 4%
NDC: 72934-2132 | Form: CREAM
Manufacturer: Sincerus Florida LLC
Category: prescription | Type: HUMAN PRESCRIPTION DRUG LABEL
Date: 20190513

ACTIVE INGREDIENTS: KETOCONAZOLE 2 g/100 g; NIACINAMIDE 4 g/100 g

KETOCONAZOLE 2% / NIACINAMIDE 4%